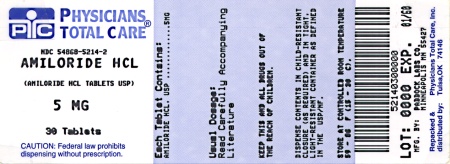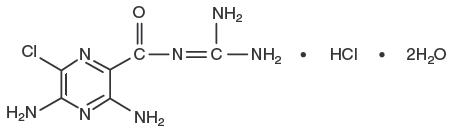 DRUG LABEL: AMILORIDE HYDROCHLORIDE
NDC: 54868-5214 | Form: TABLET
Manufacturer: Physicians Total Care, Inc.
Category: prescription | Type: HUMAN PRESCRIPTION DRUG LABEL
Date: 20090630

ACTIVE INGREDIENTS: AMILORIDE HYDROCHLORIDE 5 mg/1 1
INACTIVE INGREDIENTS: LACTOSE; MAGNESIUM STEARATE

Amiloride HCl Tablets, USP

DESCRIPTION

Amiloride HCl, an antikaliuretic-diuretic agent, is a pyrazine-carbonyl-guanidine that is unrelated chemically to other known antikaliuretic or diuretic agents. It is the salt of a moderately strong base (pKa 8.7). It is designated chemically as 3,5-diamino-6-chloro-N-(diaminomethylene) pyrazinecarboxamide monohydrochloride, dihydrate and has a molecular weight of 302.12. Its empirical formula is C6H8ClN7O•HCl•2H2O and its structural formula is:

Amiloride HCl is available for oral use as tablets containing 5 mg of anhydrous amiloride HCl. Each tablet contains the following inactive ingredients: calcium phosphate, lactose, magnesium stearate and starch.

CLINICAL PHARMACOLOGY

Amiloride HCl is a potassium-conserving (antikaliuretic) drug that possesses weak (compared with thiazide diuretics) natriuretic, diuretic, and antihypertensive activity. These effects have been partially additive to the effects of thiazide diuretics in some clinical studies. When administered with a thiazide or loop diuretic, amiloride HCl has been shown to decrease the enhanced urinary excretion of magnesium which occurs when a thiazide or loop diuretic is used alone. Amiloride HCl has potassium-conserving activity in patients receiving kaliuretic-diuretic agents.

Amiloride HCl is not an aldosterone antagonist and its effects are seen even in the absence of aldosterone.

Amiloride HCl exerts its potassium sparing effect through the inhibition of sodium reabsorption at the distal convoluted tubule, cortical collecting tubule and collecting duct; this decreases the net negative potential of the tubular lumen and reduces both potassium and hydrogen secretion and their subsequent excretion. This mechanism accounts in large part for the potassium sparing action of amiloride.

Amiloride HCl usually begins to act within 2 hours after an oral dose. Its effect on electrolyte excretion reaches a peak between 6 and 10 hours and lasts about 24 hours. Peak plasma levels are obtained in 3 to 4 hours and the plasma half-life varies from 6 to 9 hours. Effects on electrolytes increase with single doses of amiloride HCl up to approximately 15 mg.

Amiloride HCl is not metabolized by the liver but is excreted unchanged by the kidneys. About 50 percent of a 20 mg dose of amiloride HCl is excreted in the urine and 40 percent in the stool within 72 hours. Amiloride HCl has little effect on glomerular filtration rate or renal blood flow. Because amiloride HCl is not metabolized by the liver, drug accumulation is not anticipated in patients with hepatic dysfunction, but accumulation can occur if the hepatorenal syndrome develops.

INDICATIONS AND USAGE

Amiloride HCl is indicated as adjunctive treatment with thiazide diuretics or other kaliuretic-diuretic agents in congestive heart failure or hypertension to:

1. help restore normal serum potassium levels in patients who develop hypokalemia on the kaliuretic diuretic
2. prevent development of hypokalemia in patients who would be exposed to particular risk if hypokalemia were to develop, e.g., digitalized patients or patients with significant cardiac arrhythmias.

The use of potassium-conserving agents is often unnecessary in patients receiving diuretics for uncomplicated essential hypertension when such patients have a normal diet. Amiloride HCl has little additive diuretic or antihypertensive effect when added to a thiazide diuretic.

Amiloride HCl should rarely be used alone. It has weak (compared with thiazides) diuretic and antihypertensive effects. Used as single agents, potassium sparing diuretics, including amiloride HCl, result in an increased risk of hyperkalemia (approximately 10% with amiloride). Amiloride HCl should be used alone only when persistent hypokalemia has been documented and only with careful titration of the dose and close monitoring of serum electrolytes.

CONTRAINDICATIONS

Hyperkalemia

Amiloride HCl should not be used in the presence of elevated serum potassium levels (greater than 5.5 mEq per liter).

Antikaliuretic Therapy or Potassium Supplementation

Amiloride HCl should not be given to patients receiving other potassium-conserving agents, such as spironolactone or triamterene. Potassium supplementation in the form of medication, potassium-containing salt substitutes or a potassium-rich diet should not be used with amiloride HCl except in severe and/or refractory cases of hypokalemia. Such concomitant therapy can be associated with rapid increases in serum potassium levels. If potassium supplementation is used, careful monitoring of the serum potassium level is necessary.

Impaired Renal Function

Anuria, acute or chronic renal insufficiency, and evidence of diabetic nephropathy are contraindications to the use of amiloride HCl. Patients with evidence of renal functional impairment (blood urea nitrogen [BUN] levels over 30 mg per 100 mL or serum creatinine levels over 1.5 mg per 100 mL) or diabetes mellitus should not receive the drug without careful, frequent and continuing monitoring of serum electrolytes, creatinine, and BUN levels. Potassium retention associated with the use of an antikaliuretic agent is accentuated in the presence of renal impairment and may result in the rapid development of hyperkalemia.

Hypersensitivity

Amiloride HCl is contraindicated in patients who are hypersensitive to this product.

WARNINGS

Hyperkalemia

BOXED WARNING

Like other potassium-conserving agents, amiloride may cause hyperkalemia (serum potassium levels greater than 5.5 mEq per liter) which, if uncorrected, is potentially fatal. Hyperkalemia occurs commonly (about 10%) when amiloride is used without a kaliuretic diuretic. This incidence is greater in patients with renal impairment, diabetes mellitus (with or without recognized renal insufficiency), and in the elderly. When amiloride HCl is used concomitantly with a thiazide diuretic in patients without these complications, the risk of hyperkalemia is reduced to about 1-2 percent. It is thus essential to monitor serum potassium levels carefully in any patient receiving amiloride, particularly when it is first introduced, at the time of diuretic dosage adjustments, and during any illness that could affect renal function.

The risk of hyperkalemia may be increased when potassium-conserving agents, including amiloride HCl, are administered concomitantly with an angiotensin-converting enzyme inhibitor, an angiotensin II receptor antagonist, cyclosporine or tacrolimus. (See PRECAUTIONS, Drug Interactions.) Warning signs or symptoms of hyperkalemia include paresthesias, muscular weakness, fatigue, flaccid paralysis of the extremities, bradycardia, shock, and ECG abnormalities. Monitoring of the serum potassium level is essential because mild hyperkalemia is not usually associated with an abnormal ECG.

When abnormal, the ECG in hyperkalemia is characterized primarily by tall, peaked T waves or elevations from previous tracings. There may also be lowering of the R wave and increased depth of the S wave, widening and even disappearance of the P wave, progressive widening of the QRS complex, prolongation of the PR interval, and ST depression.

Treatment of hyperkalemia:

If hyperkalemia occurs in patients taking amiloride HCl, the drug should be discontinued immediately. If the serum potassium level exceeds 6.5 mEq per liter, active measures should be taken to reduce it. Such measures include the intravenous administration of sodium bicarbonate solution or oral or parenteral glucose with a rapid-acting insulin preparation. If needed, a cation exchange resin such as sodium polystyrene sulfonate may be given orally or by enema. Patients with persistent hyperkalemia may require dialysis.

Diabetes Mellitus

In diabetic patients, hyperkalemia has been reported with the use of all potassium-conserving diuretics, including amiloride HCl, even in patients without evidence of diabetic nephropathy. Therefore, amiloride HCl should be avoided, if possible, in diabetic patients and, if it is used, serum electrolytes and renal function must be monitored frequently.

Amiloride HCl should be discontinued at least three days before glucose tolerance testing.

Metabolic or Respiratory Acidosis

Antikaliuretic therapy should be instituted only with caution in severely ill patients in whom respiratory or metabolic acidosis may occur, such as patients with cardiopulmonary disease or poorly controlled diabetes. If amiloride HCl is given to these patients, frequent monitoring of acid-base balance is necessary. Shifts in acid-base balance alter the ratio of extracellular/intracellular potassium, and the development of acidosis may be associated with rapid increases in serum potassium levels.

PRECAUTIONS

General

Electrolyte Imbalance and BUN Increases

Hyponatremia and hypochloremia may occur when amiloride HCl is used with other diuretics and increases in BUN levels have been reported. These increases usually have accompanied vigorous fluid elimination, especially when diuretic therapy was used in seriously ill patients, such as those who had hepatic cirrhosis with ascites and metabolic alkalosis, or those with resistant edema. Therefore, when amiloride HCl is given with other diuretics to such patients, careful monitoring of serum electrolytes and BUN levels is important. In patients with pre-existing severe liver disease, hepatic encephalopathy, manifested by tremors, confusion, and coma, and increased jaundice, have been reported in association with diuretics, including amiloride HCl.

Drug Interactions

When amiloride HCl is administered concomitantly with an angiotensin-converting enzyme inhibitor, an angiotensin II receptor antagonist, cyclosporine or tacrolimus, the risk of hyperkalemia may be increased. Therefore, if concomitant use of these agents is indicated because of demonstrated hypokalemia, they should be used with caution and with frequent monitoring of serum potassium. (See WARNINGS.)

Lithium generally should not be given with diuretics because they reduce its renal clearance and add a high risk of lithium toxicity. Read circulars for lithium preparations before use of such concomitant therapy.

In some patients, the administration of a non-steroidal anti-inflammatory agent can reduce the diuretic, natriuretic, and antihypertensive effects of loop, potassium-sparing and thiazide diuretics. Therefore, when amiloride HCl and non-steroidal anti-inflammatory agents are used concomitantly, the patient should be observed closely to determine if the desired effect of the diuretic is obtained. Since indomethacin and potassium-sparing diuretics, including amiloride HCl, may each be associated with increased serum potassium levels, the potential effects on potassium kinetics and renal function should be considered when these agents are administered concurrently.

Carcinogenicity, Mutagenicity, Impairment of Fertility

There was no evidence of a tumorigenic effect when amiloride HCl was administered for 92 weeks to mice at doses up to 10 mg/kg/day (25 times the maximum daily human dose). Amiloride HCl has also been administered for 104 weeks to male and female rats at doses up to 6 and 8 mg/kg/day (15 and 20 times the maximum daily dose for humans, respectively) and showed no evidence of carcinogenicity.

Amiloride HCl was devoid of mutagenic activity in various strains of Salmonella typhimurium with or without a mammalian liver microsomal activation system (Ames test).

Pregnancy

Pregnancy Category B.

Teratogenicity studies with amiloride HCl in rabbits and mice given 20 and 25 times the maximum human dose, respectively, revealed no evidence of harm to the fetus, although studies showed that the drug crossed the placenta in modest amounts. Reproduction studies in rats at 20 times the expected maximum daily dose for humans showed no evidence of impaired fertility. At approximately 5 or more times the expected maximum daily dose for humans, some toxicity was seen in adult rats and rabbits and a decrease in rat pup growth and survival occurred.

There are, however, no adequate and well-controlled studies in pregnant women. Because animal reproduction studies are not always predictive of human response, this drug should be used during pregnancy only if clearly needed.

Nursing Mothers

Studies in rats have shown that amiloride is excreted in milk in concentrations higher than those found in blood, but it is not known whether amiloride HCl is excreted in human milk. Because many drugs are excreted in human milk and because of the potential for serious adverse reactions in nursing infants from amiloride HCl, a decision should be made whether to discontinue nursing or to discontinue the drug, taking into account the importance of the drug to the mother.

Pediatric Use

Safety and effectiveness in pediatric patients have not been established.

Geriatric Use

Clinical studies of amiloride HCl did not include sufficient numbers of subjects aged 65 and over to determine whether they respond differently from younger subjects. Other reported clinical experience has not identified differences in responses between the elderly and younger patients. In general, dose selection for an elderly patient should be cautious, usually starting at the low end of the dosing range, reflecting the greater frequency of decreased hepatic, renal or cardiac function, and of concomitant disease or other drug therapy.

This drug is known to be substantially excreted by the kidney, and the risk of toxic reactions to this drug may be greater in patients with impaired renal function. Because elderly patients are more likely to have decreased renal function, care should be taken in dose selection, and it may be useful to monitor renal function. (See CONTRAINDICATIONS, Impaired Renal Function.)

ADVERSE REACTIONS

Amiloride HCl is usually well tolerated and, except for hyperkalemia (serum potassium levels greater than 5.5 mEq per liter — see WARNINGS), significant adverse effects have been reported infrequently. Minor adverse reactions were reported relatively frequently (about 20%) but the relationship of many of the reports to amiloride HCl is uncertain and the overall frequency was similar in hydrochlorothiazide treated groups. Nausea/anorexia, abdominal pain, flatulence, and mild skin rash have been reported and probably are related to amiloride. Other adverse experiences that have been reported with amiloride are generally those known to be associated with diuresis, or with the underlying disease being treated.

The adverse reactions for amiloride HCl listed in the following table have been arranged into two groups: (1) incidence greater than one percent; and (2) incidence one percent or less. The incidence for group (1) was determined from clinical studies conducted in the United States (837 patients treated with amiloride HCl). The adverse effects listed in group (2) include reports from the same clinical studies and voluntary reports since marketing. The probability of a causal relationship exists between amiloride HCl and these adverse reactions, some of which have been reported only rarely.

Incidence >1% | Incidence ≤1%
Body as a Whole
Headache [Reactions occurring in 3% to 8% of patients treated with amiloride HCl. (Those reactions occurring in less than 3% of the patients are unmarked.)] Weakness Fatigability | Back pain Chest pain Neck/shoulder ache Pain, extremities
Cardiovascular
None | Angina pectoris Orthostatic hypotension Arrhythmia Palpitation
Digestive
Nausea/anorexia Diarrhea Vomiting Abdominal pain Gas pain Appetite changes Constipation | Jaundice GI bleeding Abdominal fullness GI disturbance Thirst Heartburn Flatulence Dyspepsia
Metabolic
Elevated serum potassium levels (>5.5 mEq per liter) [See WARNINGS.] | None
Skin
None | Skin rash Itching Dryness of mouth Pruritus Alopecia
Musculoskeletal
Muscle cramps | Joint pain Leg ache
Nervous
Dizziness Encephalopathy | Paresthesia Tremors Vertigo
Psychiatric
None | Nervousness Mental confusion Insomnia Decreased libido Depression Somnolence
Respiratory
Cough Dyspnea | Shortness of breath
Special Senses
None | Visual disturbances Nasal congestion Tinnitus Increased intraocular pressure
Urogenital
Impotence | Polyuria Dysuria Urinary frequency Bladder spasms Gynecomastia

Causal Relationship Unknown

Other reactions have been reported but occurred under circumstances where a causal relationship could not be established. However, in these rarely reported events, that possibility cannot be excluded. Therefore, these observations are listed to serve as alerting information to physicians.

Activation of probable pre-existing peptic ulcer

Aplastic anemia

Neutropenia

Abnormal liver function

OVERDOSAGE

No data are available in regard to overdosage in humans.

The oral LD50 of amiloride hydrochloride (calculated as the base) is 56 mg/kg in mice and 36 to 85 mg/kg in rats, depending on the strain.

It is not known whether the drug is dialyzable.

The most likely signs and symptoms to be expected with overdosage are dehydration and electrolyte imbalance. These can be treated by established procedures. Therapy with amiloride HCl should be discontinued and the patient observed closely. There is no specific antidote. Emesis should be induced or gastric lavage performed. Treatment is symptomatic and supportive. If hyperkalemia occurs, active measures should be taken to reduce the serum potassium levels.

DOSAGE AND ADMINISTRATION

Amiloride HCl should be administered with food.

Amiloride HCl, one 5 mg tablet daily, should be added to the usual antihypertensive or diuretic dosage of a kaliuretic diuretic. The dosage may be increased to 10 mg per day, if necessary. More than two 5 mg tablets of amiloride HCl daily usually are not needed, and there is little controlled experience with such doses. If persistent hypokalemia is documented with 10 mg, the dose can be increased to 15 mg, then 20 mg, with careful monitoring of electrolytes.

In treating patients with congestive heart failure after an initial diuresis has been achieved, potassium loss may also decrease and the need for amiloride HCl should be re-evaluated. Dosage adjustment may be necessary. Maintenance therapy may be on an intermittent basis.

If it is necessary to use amiloride HCl alone (See INDICATIONS), the starting dosage should be one 5 mg tablet daily. This dosage may be increased to 10 mg per day, if necessary. More than two 5 mg tablets usually are not needed, and there is little controlled experience with such doses. If persistent hypokalemia is documented with 10 mg, the dose can be increased to 15 mg, then 20 mg, with careful monitoring of electrolytes.

HOW SUPPLIED

Amiloride HCl Tablets, 5 mg, are off-white to light yellow, diamond-shaped, compressed tablets, embossed with "P291". They are supplied in

Bottles of 10 | NDC 54868-5214-3
Bottles of 20 | NDC 54868-5214-1
Bottles of 30 | NDC 54868-5214-2
Bottles of 60 | NDC 54868-5214-0

STORAGE

Protect from moisture, freezing and excessive heat. Store at 20° to 25°C (68° to 77°F) [see USP Controlled Room Temperature]

Mfg by: Paddock Laboratories, Inc.
Minneapolis, MN 55427
(11-08)

Relabeling and Repackaging by:
Physicians Total Care, Inc.
Tulsa, OK 74146

PRINCIPAL DISPLAY PANEL - 5 mg Tablets

AMILORIDE HCl TABLETS, USP

5 mg (Anhydrous equivalent)

Rx ONLY

Dispense in a tight container. Keep container tightly
closed. Protect from moisture, freezing and
excessive heat. Store at 20° to 25°C (68° to 77°F)
[see USP Controlled Room Temperature]